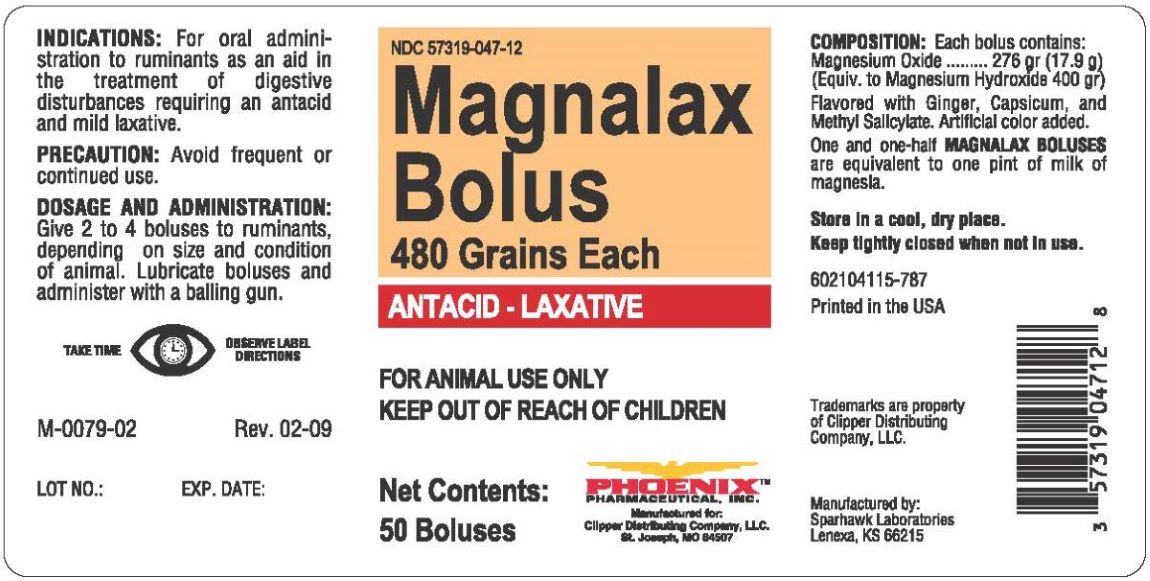 DRUG LABEL: Magnalax Bolus
NDC: 57319-047 | Form: TABLET
Manufacturer: Clipper Distributing Company, LLC
Category: animal | Type: OTC ANIMAL DRUG LABEL
Date: 20240606

ACTIVE INGREDIENTS: MAGNESIUM OXIDE 276 g/1 1

Magnalax Bolus

INDICATIONS AND USAGE

ANTIACID-LAXATIVE

FOR ANIMAL USE ONLY

KEEP OUT OF REACH OF CHILDREN

INDICATIONS

For oral administration as an aid in the treatment of digestive disturbances requiring an antacid or mild laxative.

PRECAUTION

Avoid frequent or continued use.

DOSAGE AND ADMINISTRATION

Give 2 to 4 boluses to ruminants, depending on size and condition of animal. Lubricate boluses and adminster with a balling gun.

COMPOSITION

Each bolus contains:

Magnesium Oxide ...... 276 grs. (17.9 g)
(Equiv. to Magnesium Hydroxide, 400 grs.)
Flavored with Ginger, Capsicum, and Methyl Salicylate. Artificial color added. One and one-half MAGNALAX BOLUS are equivalent to one pint of milk of magnesia.

STORAGE AND HANDLING

Store in a cool, dry place.

Keep tightly closed when not in use.

TAKE TIME TO OBSERVE LABEL DIRECTIONS